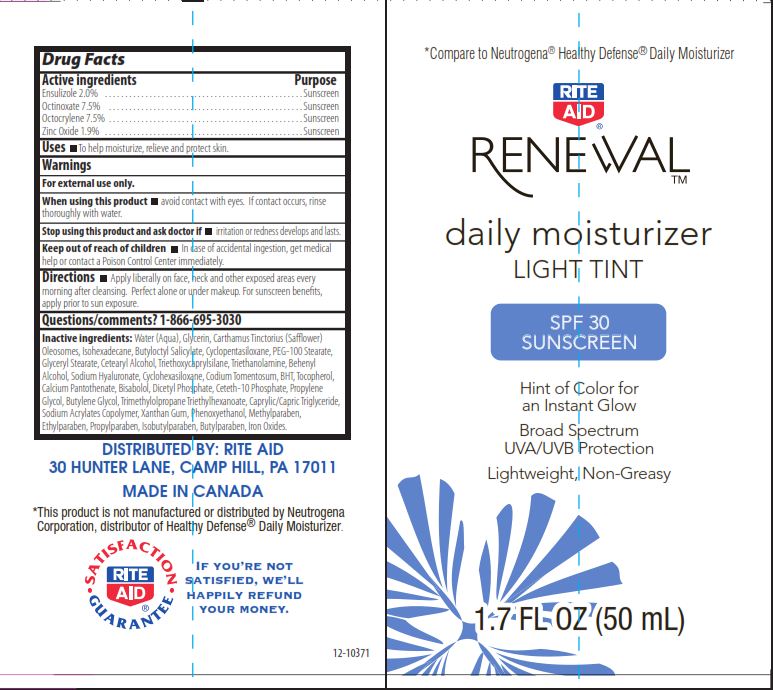 DRUG LABEL: RITE AID RENEWAL
NDC: 11822-3410 | Form: LOTION
Manufacturer: RITE AID CORPORATION
Category: otc | Type: HUMAN OTC DRUG LABEL
Date: 20110721

ACTIVE INGREDIENTS: ENSULIZOLE 2 mL/100 mL; OCTINOXATE 7.5 mL/100 mL; OCTOCRYLENE 7.5 mL/100 mL; ZINC OXIDE 1.9 mL/100 mL
INACTIVE INGREDIENTS: WATER; GLYCERIN; SAFFLOWER; ISOHEXADECANE; BUTYLOCTYL SALICYLATE; CYCLOMETHICONE 5; PEG-100 STEARATE; GLYCERYL MONOSTEARATE; CETOSTEARYL ALCOHOL; TRIETHOXYCAPRYLYLSILANE; TROLAMINE; BEHENYL PHOSPHATE; HYALURONATE SODIUM; CYCLOMETHICONE 6; CODIUM TOMENTOSUM; BUTYLATED HYDROXYTOLUENE; TOCOPHEROL; CALCIUM PANTOTHENATE; .ALPHA.-BISABOLOL, (+/-)-; DIHEXADECYL PHOSPHATE; CETETH-10 PHOSPHATE; PROPYLENE GLYCOL; 1,2-BUTANEDIOL; TRIMETHYLOLPROPANE TRIETHYLHEXANOATE; CAPRYLIC/CAPRIC MONO/DIGLYCERIDES; ANISACRIL; GUAR GUM; PHENOXYETHANOL; METHYLPARABEN; ETHYLPARABEN; PROPYLPARABEN; ISOBUTYLPARABEN; BUTYLPARABEN; FERRIC OXIDE RED

DRUG FACTS

ACTIVE INGREDIENT

ENSULIZOLE 2.0%, OCTINOXATE 7.5%, OCTOCRYLENE 7.5%, ZINC OXIDE 1.9%

PURPOSE

SUNSCREEN

USES

TO HELP MOISTURIZE, RELIEVE AND PROTECT SKIN

WARNINGS

FOR EXTERNAL USE ONLY

WHEN USING THIS PRODUCT

AVOID CONTACT WITH EYES. IF CONTACT OCCURS, RINSE THOROUGHLY WITH WATER.

STOP USING THIS PRODUCT AND ASK DOCTOR IF

IF IRRITATION OR REDNESS DEVELOPS AND LASTS

KEEP OUT OF REACH OF CHILDREN

IN CASE OF ACCIDENTAL INGESTION, GET MEDICAL HELP OR CONTACT A POISON CONTROL IMMEDIATELY

DIRECTIONS

APPLY LIBERALLY ON FACE, NECK AND OTHER EXPOSED AREAS EVERY MORNING AFTER CLEANSING. PERFECT ALONE OR UNDER MAKEUP. FOR SUNSCREEN BENEFITS, APPLY PRIOR TO SUN EXPOSURE.

QUESTIONS OR COMMENTS

1-866-695-3030

INACTIVE INGREDIENTS

WATER, GLYCERIN,CARTHAMUS TINCTORIUS (SAFFLOWER) OLEOSOMES, ISOHEXADECANE, BUTYLOCTYL SALICYLATE, CYCLOPENTASILOXANE, PEG-100 STEARATE, GLYCERYL STEARATE, CETEARYL ALCOHOL, TRIETHOXYCAPRYLSILANE, TRIETHANOLAMINE, BEHENYL ALCOHOL, SODIUM HYALURONATE, CYCLOHEXASILOXANE, CODIUM TOMENTOSUM, BHT, TOCOPHEROL, CALCIUM PENTOTHENATE, BISABOLOL, DICETYL PHOSPHATE, CETETH-10 PHOSPHATE, PROPYLENE GLYCOL, BUTYLENE GLYCOL, TRIMETHYLOLPROPANE TRIETHYLHEXANOATE, CAPRYLIC/CAPRIC TRIGLYCERIDE, SODIUM ACRYLATES COPOLYMER, XANTHAN GUM, PHENOXYETHANOL, METHYLPARABEN, ETHYLPARABEN, PROPYLPARABEN, ISOBUTYLPARABEN, BUTYLPARABEN, IRON OXIDES